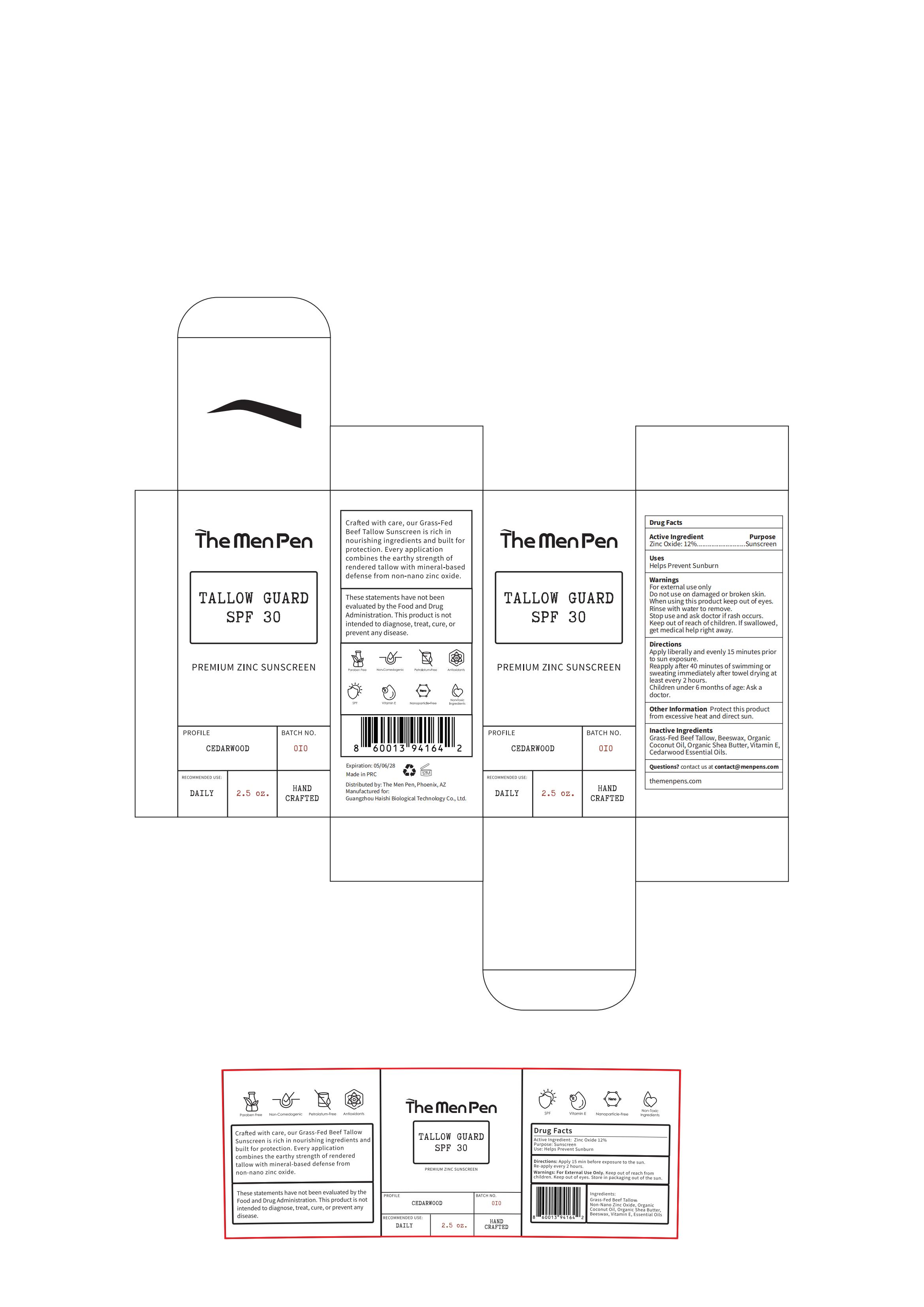 DRUG LABEL: The Men Pen TALLOW GUARD SPF 30 PREMIUM ZINC SUNSCREEN
NDC: 60771-0026 | Form: STICK
Manufacturer: Guangzhou Haishi Biological Technology Co., Ltd.
Category: otc | Type: HUMAN OTC DRUG LABEL
Date: 20250724

ACTIVE INGREDIENTS: ZINC OXIDE 12 g/100 g
INACTIVE INGREDIENTS: SHEA BUTTER; TALLOW; BEESWAX; COCONUT OIL

The Men Pen TALLOW GUARD SPF 30 PREMIUM ZINC SUNSCREEN

ACTIVE INGREDIENT

Zinc oxide 12%

PURPOSE

Sunscreen

INDICATIONS AND USAGE

Apply liberally and evenly 15 minutes priorto sun exposure.Reapply after 40 minutes of swimming orsweatingimmediately after towel drying atleast every 2 hours.

WARNINGS

For external use only

Stop use and ask doctor if rash occurs.
Rinse with water to remove.

Do not use on damaged or broken skin.

When using this product keep out of eyes.

KEEP OUT OF REACH OF CHILDREN

Keep out ofreach ofchildren. if swallowed get medical help right away.

DOSAGE AND ADMINISTRATION

Apply evenly on the skin

INACTIVE INGREDIENT

Beeswax 51.5%
Tallow 20%
Coconut Oil 10%
Shea Butter 6%
Cedar wood Essential Oil 0.5%